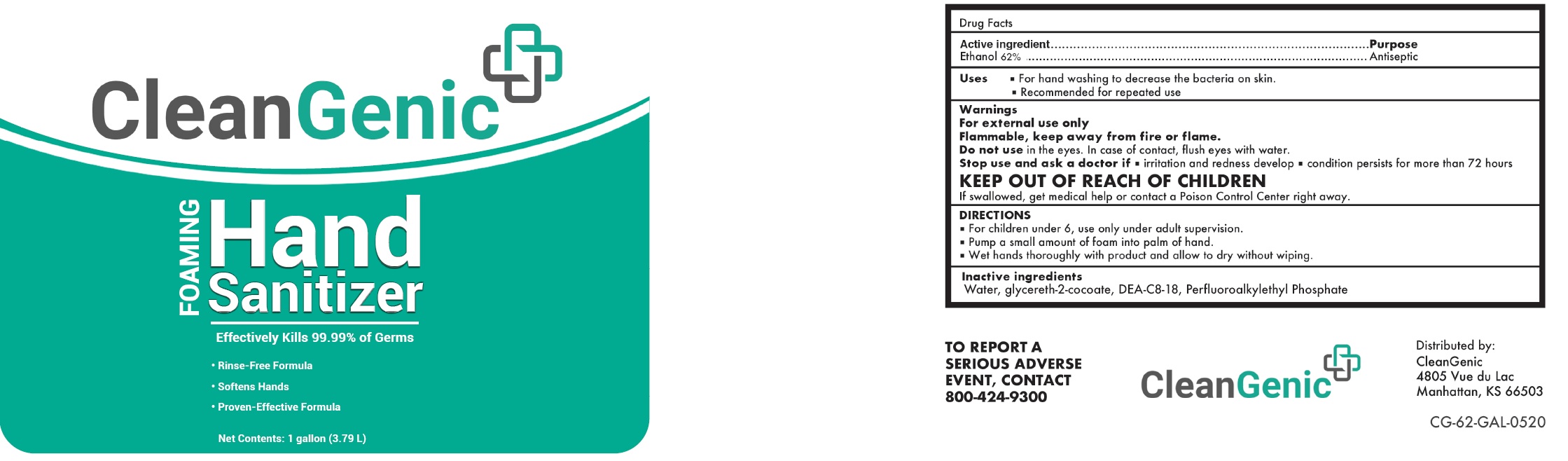 DRUG LABEL: CleanGenic Foaming Hand Sanitizer
NDC: 81385-000 | Form: LIQUID
Manufacturer: CleanGenic, LLC
Category: otc | Type: HUMAN OTC DRUG LABEL
Date: 20231028

ACTIVE INGREDIENTS: ALCOHOL 62 mL/100 mL
INACTIVE INGREDIENTS: WATER; GLYCERETH-2 COCOATE; DIETHANOLAMINE BIS(C8-C18 PERFLUOROALKYLETHYL)PHOSPHATE

CleanGenic Foaming Hand Sanitizer

Active ingredient

Ethanol 62%

Purpose

Antiseptic

Uses

- For hand washing to decrease the bacteria on skin.
- Recommended for repeated use

Warnings

For external use only Flammable, keep away from fire or flame.

Do not use

in the eyes. In case of contact, flush eyes with water.

Stop use and ask a doctor if

- irritation and redness develop
- condition persists for more than 72 hours

KEEP OUT OF REACH OF CHILDREN

If swallowed, get medical help or contact a Poison Control Center right away.

DIRECTIONS

- For children under 6, use only under adult supervision.
- Pump a small amount of foam into palm of hand.
- Wet hands thoroughly with product and allow to dry without wiping.

Inactive ingredients

Water, glycereth-2-cocoate, DEA-C8-18 Perfluoroalkylethyl Phosphate